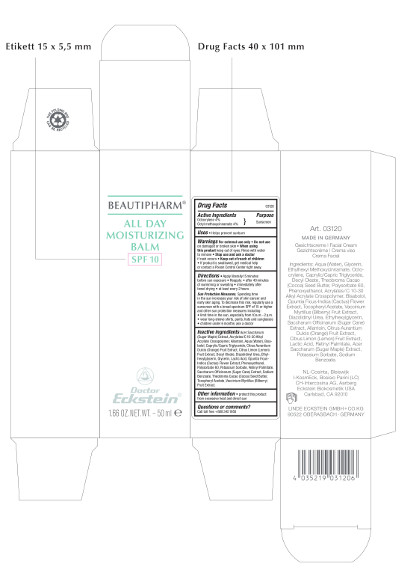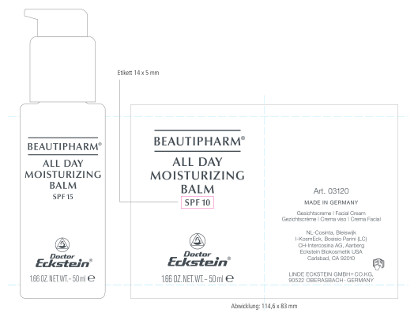 DRUG LABEL: Beautipharm All Day Moisturizing Balm
NDC: 6889-0312 | Form: CREAM
Manufacturer: Linde Eckstein GmbH + Co. KG
Category: otc | Type: HUMAN OTC DRUG LABEL
Date: 20161005

ACTIVE INGREDIENTS: OCTINOXATE 2 g/50 mL; OCTOCRYLENE 2 g/50 mL
INACTIVE INGREDIENTS: WATER 20.625 g/50 mL; GLYCERIN 5 g/50 mL; MEDIUM-CHAIN TRIGLYCERIDES 5 g/50 mL; DECYL OLEATE 5 g/50 mL; COCOA BUTTER 5 g/50 mL; POLYSORBATE 60 1.5 g/50 mL; PHENOXYETHANOL 1.0 g/50 mL; CARBOMER COPOLYMER TYPE B (ALLYL PENTAERYTHRITOL CROSSLINKED) 1.0 g/50 mL; .ALPHA.-BISABOLOL, (+)- 0.5 g/50 mL; OPUNTIA FICUS-INDICA FLOWER 0.5 g/50 mL; .ALPHA.-TOCOPHEROL ACETATE, DL- 0.25 g/50 mL; BILBERRY 0.15 g/50 mL; DIAZOLIDINYL UREA 0.15 g/50 mL; ETHYLHEXYLGLYCERIN 0.15 g/50 mL; SUGARCANE 0.05 g/50 mL; ALLANTOIN 0.05 g/50 mL; ORANGE 0.015 g/50 mL; LEMON 0.015 g/50 mL; LACTIC ACID 0.015 g/50 mL; VITAMIN A PALMITATE 0.015 g/50 mL; ACER SACCHARUM BARK/SAP 0.005 g/50 mL; POTASSIUM SORBATE 0.005 g/50 mL; SODIUM BENZOATE 0.005 g/50 mL

Beautipharm® All Day Moisturizing Balm

Beautipharm® All Day Moisturizing Balm

SPF 10

1.66 OZ.NET.WT – 50 ml

Art. 03120

MADE IN GERMANY

Gesichtscreme - Facial Cream – Gezichtscrème – Crema viso – Crema Facial

Ingredients: Aqua (Water), Glycerin, Ethylhexyl Methoxycinnamate, Octocrylene, Caprylic/Capric Triglyceride, Decyl Oleate, Theobroma Cacao (Cocoa) Seed Butter, Polysorbate 60, Phenoxyethanol, Acrylates/C 10-30 Alkyl Acrylate Crosspolymer, Bisabolol, Opuntia Ficus-Indica (Cactus) Flower Extract, Tocopheryl Acetate, Vaccinium Myrtillus (Bilberry) Fruit Extract, Diazolidinyl Urea, Ethylhexylglycerin, Saccharum Officinarum (Sugar Cane) Extract, Allantoin, Citrus Aurantium Dulcis (Orange) Fruit Extract, Citrus Limon (Lemon) Fruit Extract, Lactic Acid, Retinyl Palmitate, Acer Saccharum (Sugar Maple) Extract, Potassium Sorbate, Sodium Benzoate.

NL-Cosinta, Bleiswijk

KosmEck Italia – Bosisio Parini (LC)

CH-Intercosina AG, Aarberg

Eckstein Biokosmetik USA

Carlsbad, CA 92010

LINDE ECKSTEIN GMBH+CO.KG

90522 OBERASBACH · GERMANY

Drug Facts

Active Ingredients

Octocrylene 4%

Octyl methoxycinnamate 4%

Purpose

Sunscreen

Uses

• Helps prevent sunburn

Warnings For external use only

• Do not use on damaged or broken skin

• When using this product keep out of eyes. Rinse with water to remove

• Stop use and ask a doctor if rash occurs

• Keep out of reach of children

• If product is swallowed, get medical help or contact a Poison Control Center right away.

Directions

• Apply liberally 15 minutes before sun exposure

• Reapply:

• after 40 minutes of swimming or sweating

• immediately after towel drying

• at least every 2 hours

Sun Protection Measures.

Spending time in the sun increases your risk of skin cancer and early skin aging. To decrease this risk, regularly use a sunscreen with a broad spectrum SPF of 15 or higher and other sun protection measures including:

• limit time in the sun, especially from 10 a.m. - 2 p.m.

• wear long-sleeve shirts, pants, hats and sunglasses

• children under 6 months: ask a doctor

Inactive ingredients

Acer Saccharum (Sugar Maple) Extract, Acrylates / C 10-30 Alkyl Acrylate Crosspolymer, Allantoin, Aqua (Water), Bisabolol, Caprylic/Capric Triglyceride, Citrus Aurantium Dulcis (Orange) Fruit Extract, Citrus Limon (Lemon) Fruit Extract, Decyl Oleate, Diazolidinyl Urea, Ethylhexylglycerin, Glycerin, Lactic Acid, Opuntia Ficus-Indica (Cactus) Flower Extract, Phenoxyethanol, Polysorbate 60, Potassium Sorbate, Retinyl Palmitate, Saccharum Officinarum (Sugar Cane) Extract, Sodium Benzoate, Theobroma Cacao (Cocoa) Seed Butter, Tocopheryl Acetate, Vaccinium Myrtillus (Bilberry) Fruit Extract.

Other information

• protect this product from excessive heat and direct sun

Questions or comments?

Call toll free +888 345 1950

Beautipharm® All Day Moisturizing Balm

SPF 10

1.66 OZ. NET.WT.– 50 ml

Art. 03120

MADE IN GERMANY

Gesichtscreme - Facial Cream – Gezichtscrème – Crema viso – Crema Facial

NL-Cosinta, Bleiswijk

KosmEck Italia – Bosisio Parini (LC)

CH-Intercosina AG, Aarberg

Eckstein Biokosmetik USA

Carlsbad, CA 92010

LINDE ECKSTEIN GMBH+CO.KG,

90522 OBERASBACH · GERMANY